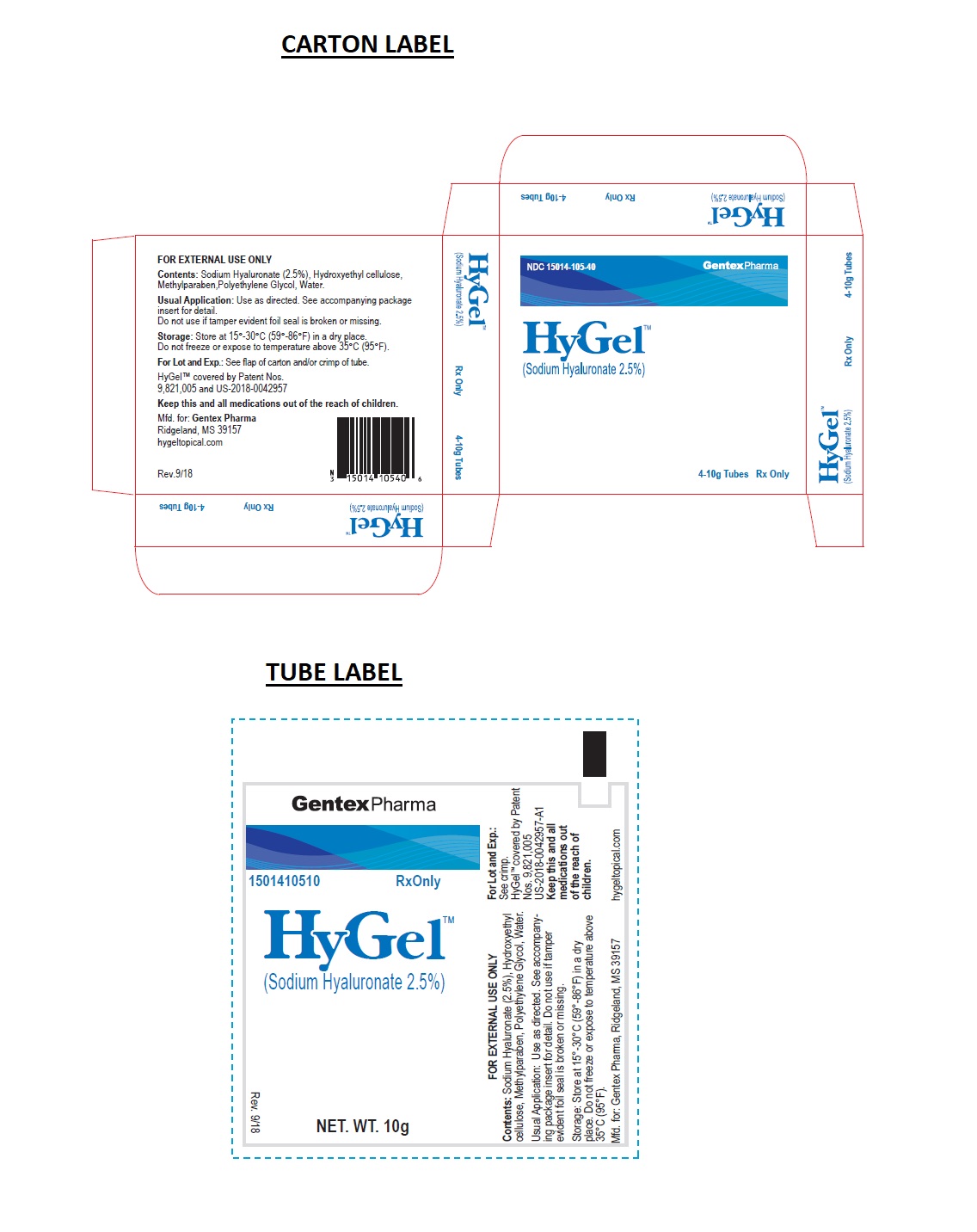 DRUG LABEL: HyGel
NDC: 15014-105
Manufacturer: Gentex Pharma
Category: other | Type: PRESCRIPTION MEDICAL DEVICE LABEL
Date: 20190911

HyGel™

HyGel™

(Sodium Hyaluronate) 2.5% Rx Only

PRODUCT DESCRIPTION

HyGel™ is a clear viscous, odorless, aqueous gel composed principally of sodium hyaluronate, a derivative salt of Hyaluronic acid. The portion of sodium hyaluronate “w/w” in the formulation is 2.5%.

Hyaluronic acid is a molecule which is normally found in various parts of the body. Hyaluronic acid used in HyGel™ is derived from a synthetic source more specifically from a bacterial fermentation process. HyGel™ serves to maintain a moist wound environment. The maintenance of a moist wound environment is widely recognized to positively contribute to wound healing process.

INGREDIENT

Sodium hyaluronate (2.5%)

OTHER INGREDIENTS

Other ingredients in HyGel™ are as follows:
Hydroxyethyl cellulose, methylparaben, as well as polyethylene glycol, and purified water, USP.

INDICATIONS FOR USE Rx Only: Under the supervision of a healthcare professional;

- HyGel™ is indicated for management of exudating wounds such as leg ulcers, pressure ulcers, diabetic ulcers, surgical wounds (post-operative and donor sites), mechanically or surgically debrided wounds, and for second degree burns.
- HyGel™ is indicated for the management and relief of burning, itching, and pain associated with various types of dermatoses; including atopic dermatitis, allergic contract dermatitis and radio-dermatitis.

CONTRAINDICATIONS

Do not administer to patients with known hyper-sensitivity to the components of this product.

WARNINGS

- The prolonged use of the product may give rise to a sensitization phenomenon. Should this occur, discontinue use of the product immediately and consult a healthcare professional.
- To prevent the possibility of cross infection, a tube of HyGel™ should be used on one patient only.
- Direct contact with the wound and the container should be avoided.
- Do not use in case of package damage.
- Do not use the product after the expiry date noted on the package.
- Keep out of reach of children.

PRECAUTIONS AND OBSERVATIONS Rx Only: Consult a healthcare professional if;

1. Signs of infection occur, increased pain, bleeding or wound drainage.
2. There is a change in wound color and/or odor.
3. The wound does not begin to show signs of healing in a few days.
4. Any other unexpected symptoms occur.

Under the supervision of a healthcare professional;

• The treatment of any leg ulcers, pressure ulcers, diabetic ulcers and surgically debrided wounds should be under the supervision of a healthcare professional.
• Appropriate supportive measures should be taken where indicated (e.g. use of graduated compression bandaging in the management of venous leg ulcers or pressure relief measures in the management of pressure ulcers).
NOTE: The control of blood glucose as well as appropriate pressure relief measures should be provided with diabetic foot ulcers.
• If the wound becomes infected, please immediately consult with a healthcare professional as to whether use of HyGel™ should be continued.
• HyGel™ is for external use only.

HOW TO USE

For Wounds;
1. First, clean the ulcer or other wound with normal saline solution (other cleaning agents are not recommended). Normal saline solution can be obtained through your location pharmacy.
NOTE: Debridement (surgical cleaning) of the wound may be performed at the discretion of the healthcare professional.
2. Remove excess moisture with a dry gauze.
3. Apply HyGel™ liberally into the cavity of the ulcer or wound site and the surrounding area.
4. Apply a non-stick gauze dressing over the wound site.
NOTE: Once HyGel™ is applied the gel should not be touched.
5. Finally, wrap a self-adhesive bandage over the non-stick gauze dressing.
6. Repeat the entire process of wound cleaning, applying HyGel™, and bandaging daily, or as needed.
7. Visit a healthcare professional as recommended.

For Dermatoses;
1. Using a few gentle strokes to smooth the gel across the skin in the same direction as hair growth, apply to the affected areas of the skin on a regular basis and as often as required.
2. If necessary, allow time for any excess to penetrate into the skin. Do not rub the skin vigorously.
3. You can apply HyGel before and after washing; showering or having a bath to help condition your skin and stop it from drying further.
4. If you are applying another topical treatment to the same areas of skin, try to avoid mixing the two products. You may choose to apply the treatments alternately, leaving sufficient time to allow the previous application to penetrate the skin.

HOW SUPPLIED

HyGel™ is available in a 10 gram single tube with tamper evident seal, NDC 15014-105-10, a carton with four 10 gram tubes with tamper evident seal, NDC 15014-105-40, and a 75 gram tube with tamper evident seal, NDC 15014-105-75. Do not use if tamper evident foil seal is broken or missing.

Lot number and expiry date are located on the crimped end of the tube.

STORAGE

Store in a cool dry place; at room temperature. Temperature should not exceed 35°C/95°F. Protect from freezing.

FURTHER INFORMATION
If further information, contact;
Gentex Pharma
121 Marketridge Drive
Ridgeland, MS 39157
Phone: (601) 990-9497
www.hygeltopical.com

Distributed by:
Gentex Pharma
121 Marketridge Drive
Ridgeland, MS 39157

HyGel is covered by US-2018-0042957-A1
HyGel is covered by Patent Filing No. 9,821,005